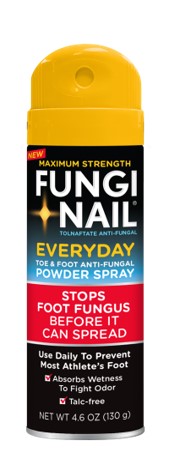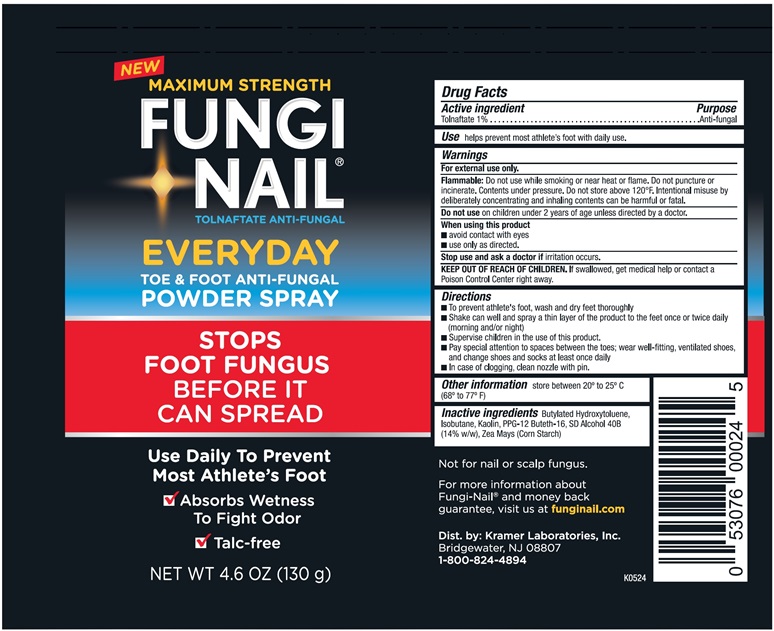 DRUG LABEL: Fungi Nail Everyday Antifungal Powder
NDC: 55505-234 | Form: SPRAY
Manufacturer: Kramer Laboratories
Category: otc | Type: HUMAN OTC DRUG LABEL
Date: 20240524

ACTIVE INGREDIENTS: Tolnaftate 1.3 g/130 g
INACTIVE INGREDIENTS: Butylated Hydroxytoluene; Isobutane; Kaolin; Ppg-12-Buteth-16; Alcohol; Zea Mays Whole

Drug Facts

ACTIVE INGREDIENT

Active Ingredient | Purpose
Tolnaftate 1% | Anti-fungal

INDICATIONS AND USAGE

Use helps prevent most athlete's foot with daily use.

Warnings

For external use only.

DO NOT USE

Flammable: Do not use while smoking or near heat or flame. Do not puncture or incinerate. Contents under pressure. Do not store above 120°F. Intentional misuse by deliberately concentrating and inhaling contents can be harmul or fatal.

Do not use on children under 2 years of age unless directed by a doctor.

When using this product
■ avoid contact with eyes
■ use only as directed.

Stop use and ask a doctor if irritation occurs.

KEEP OUT OF REACH OF CHILDREN

KEE OUT OF REACH OF CHILDREN. If swallowed, get medical help or contact a Poison Control Center right away.

Directions
■ To prevent athlete's foot, wash and dry feet thoroughly
■ Shake can well and spray a thin layer of the product to the feet once or twice daily (morning and/or night)
■ Supervise children in the use of this product.
■ Pay special attention to spaces between the toes; wear well-fitting, ventilated shoes, and change shoes and socks at least once daily
■ In case of clogging, clean nozzle with pin.

Other information store between 20° to 25°C (68° to 77°F)

INACTIVE INGREDIENT

Inactive ingredients Butylated Hydroxytoluene, Isobutane, Kaolin, PPG-12 Buteth-16, SD Alcohol 40B (14% w/w), Zea Mays (Corn Starch)

PRINCIPAL DISPLAY PANEL

NEW MAXIMUM STRENGTH
FUNGI
NAIL®
TOLNAFTATE ANTI-FUNGAL
EVERYDAY
TOE & FOOT ANTI-FUNGAL
POWDER SPRAY
STOPS
FOOT FUNGUS
BEFORE IT
CAN SPREAD
Use Daily To Prevent
Most Athlete's Foot
▪ Absorbs Wetness
To Fight Odor
▪ Talc-free
NET WT 4.6 OZ (130 g)
Not for nail or scalp fungus.
For more information about
Fungi-Nail® and money back
guarantee, visit us at funginail.com
Dist. by: Kramer Laboratories, Inc.
Bridgewater, NJ 08807
1-800-824-4894
K0524